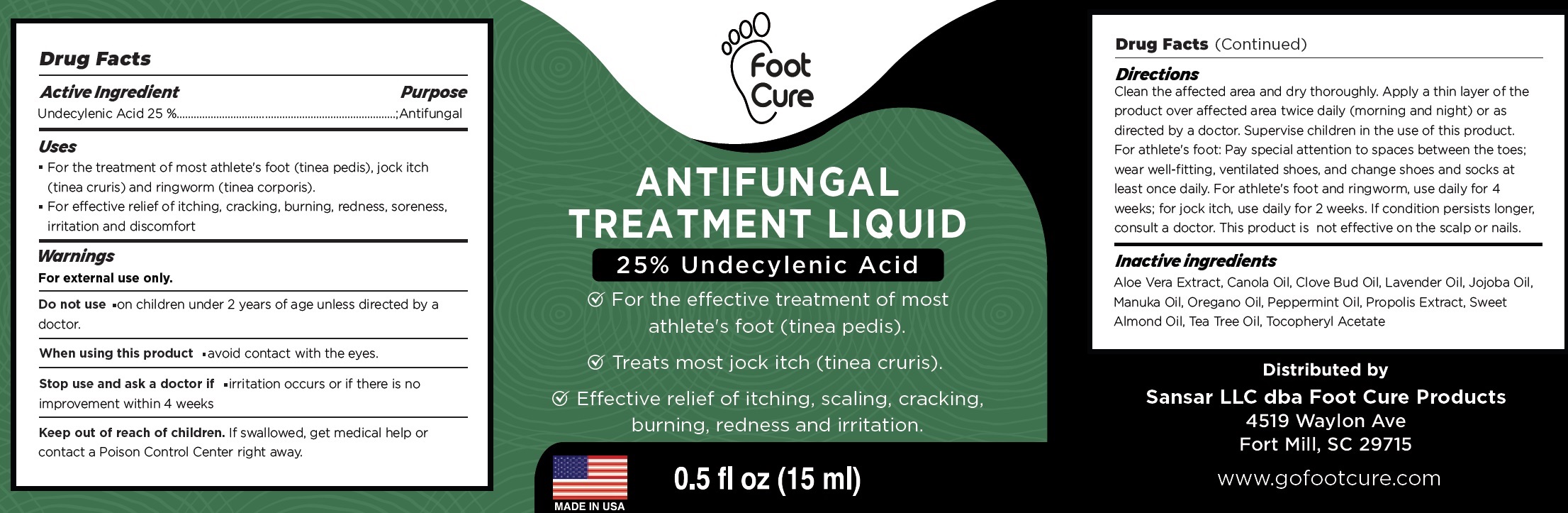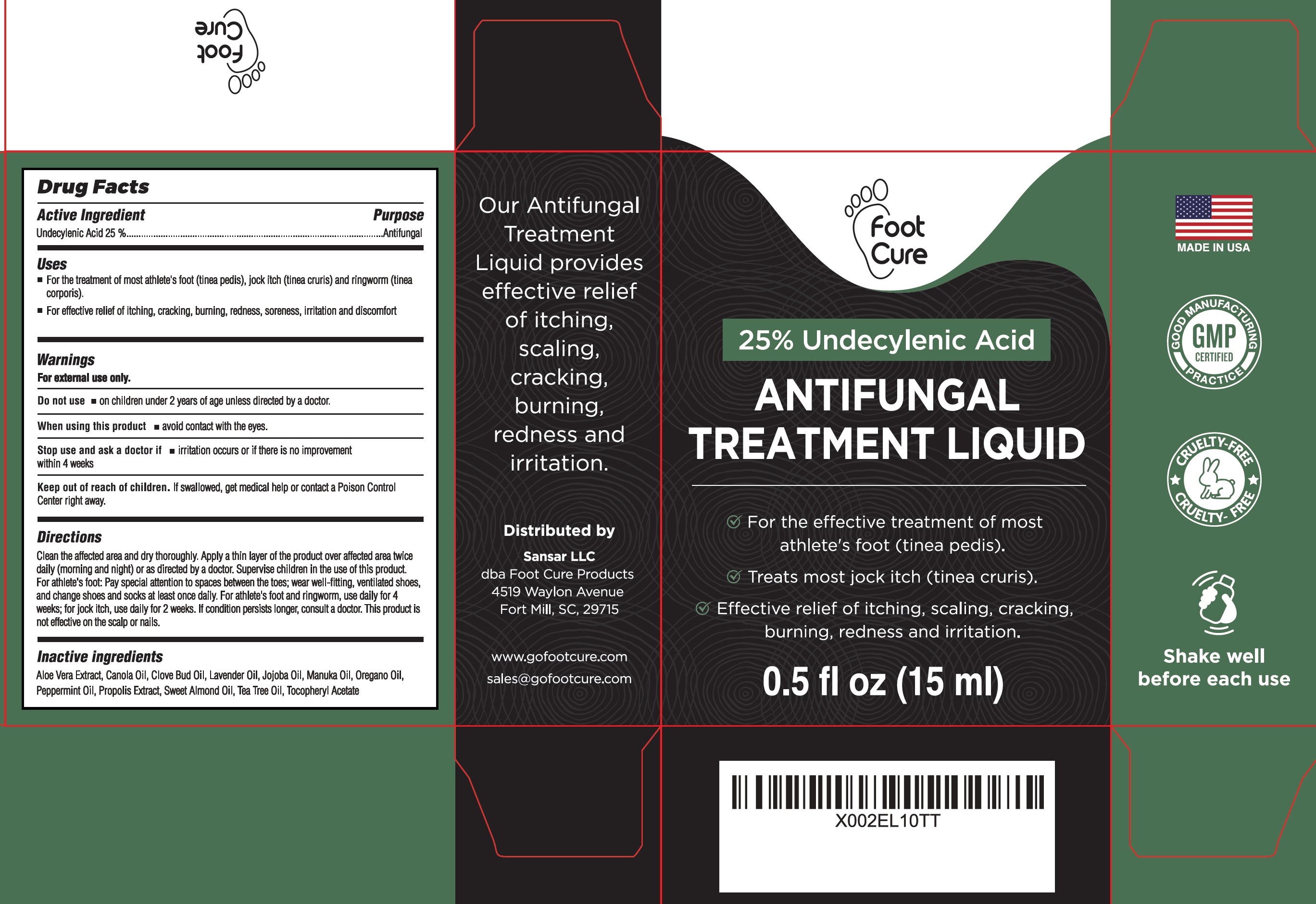 DRUG LABEL: Antifungal Treatment Liquid 25 undeclylenic Acid
NDC: 83691-000 | Form: LIQUID
Manufacturer: SANSAR, LLC
Category: otc | Type: HUMAN OTC DRUG LABEL
Date: 20250402

ACTIVE INGREDIENTS: UNDECYLENIC ACID 250 mg/1 mL
INACTIVE INGREDIENTS: ALOE VERA LEAF; CANOLA OIL; CLOVE OIL; LAVENDER OIL; JOJOBA OIL; MANUKA OIL; OREGANO LEAF OIL; PEPPERMINT OIL; PROPOLIS WAX; ALMOND OIL; TEA TREE OIL; .ALPHA.-TOCOPHEROL ACETATE

Antifungal Treatment Liquid 25% undeclylenic Acid

Active Ingredient

Undecylenic Acid 25%

Purpose

Antifungal

Uses

- For the treatment of most athlete's foot (tinea pedis), jock itch (tinea cruris) and ringworm (tinea corporis).
- For effective relief of itching, cracking, burning, redness, soreness, irritation and discomfort

Warnings

For external use only.

Do not use

- on children under 2 years of age unless directed by a doctor.

When using this product

- avoid contact with the eyes.

Stop use and ask a doctor if

- irritation occurs or if there is no improvement within 4 weeks

Keep out of reach of children.

If swallowed, get medical help or contact a Poison Control Center right away.

Directions

Clean the affected area and dry thoroughly. Apply a thin layer of the product over affected area twice daily (morning and night) or as directed by a doctor. Supervise children in the use of this product. For athlete's foot: Pay special attention to spaces between the toes; wear well-fitting, ventilated shoes, and change shoes and socks at least once daily. For athlete's foot and ringworm, use daily for 4 weeks; for jock itch, use daily for 2 weeks.If condition persists longer, consult a doctor. This product is not effective on the scalp or nails.

Inactive ingredients

Aloe Vera Extract, Canola Oil, Clove Bud Oil, Lavender Oil, Manuka Oil, Oregano Oil, Peppermint Oil, Propolis Extract, Sweet Almond Oil, Tea Tree Oil, Tocopheryl Acetate